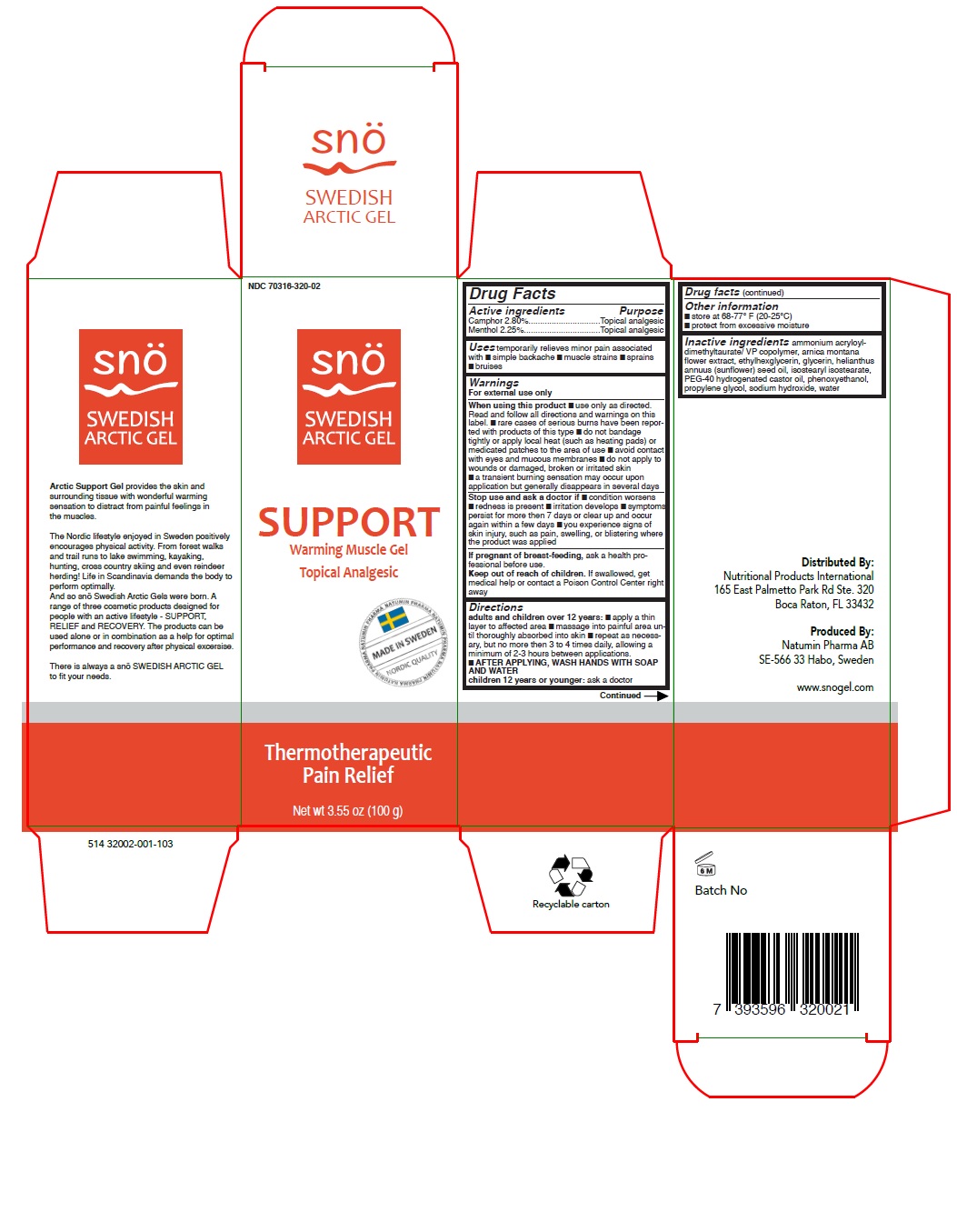 DRUG LABEL: Sno Swedish Arctic Gel Support
NDC: 70316-320 | Form: GEL
Manufacturer: Natumin Pharma AB
Category: otc | Type: HUMAN OTC DRUG LABEL
Date: 20160102

ACTIVE INGREDIENTS: CAMPHOR (SYNTHETIC) 2.8 g/100 g; MENTHOL, UNSPECIFIED FORM 2.25 g/100 g
INACTIVE INGREDIENTS: AMMONIUM ACRYLOYLDIMETHYLTAURATE/VP COPOLYMER; ARNICA MONTANA FLOWER; ETHYLHEXYLGLYCERIN; SUNFLOWER OIL; ISOSTEARYL ISOSTEARATE; PHENOXYETHANOL; WATER; GLYCERIN; SODIUM HYDROXIDE; POLYOXYL 40 HYDROGENATED CASTOR OIL; PROPYLENE GLYCOL

Drug Facts

Active Ingredients

Camphor 2.8%

Menthol 2.25%

Purpose

Topical Analgesic

Uses

temporarily relieves minor pain associated with

- simple backache
- muscle strains
- sprains
- bruises

Warnings

For external use only

When using this product us only as directed

Read and follow all directions and warnings on this label

Rare cases of serious burns have been reported with products of this type

Do not bandage tightly or apply local heat (such as heating pads) or medicated patches to the area of use

Avoid contact with eyes and mucous membranes

Do not apply to wounds or damaged, broken or irritated skin

A transient burning sensation may occur upon applicaiton bu generally disappears in several days

Stop use and ask doctor if

Condition worsens

Redness is present

Irritation develops

Sympotms persist for more than 7 days or clear up and occur again within a few days

You experience signs of skin injury, such as pain, swelling, or blistering where the product was applied

If pregnant or breastfeeding

Ask a health professional before use

Keep out of reach of children

If swallowed, get medical help or contact a Poison Control Center right away

Directions

Adults and children over 12 years

Apply a thin layer to affected area

massage into painful area until thoroughly absorbed into skin

repeat as necessary, but no more than 3 to 4 times daily, allowing a minimum of 2-3 hours between applications

After applying, wash hands with soap and water

Children 12 years or under, ask a doctor

Other Information

Store at 68-77°F (20-25°C)

Protect from excessive moisture

Inactive Ingredients

ammonium acryloyldimethyltaurate/ VP copolymer

arnica montana flower extract

ethylhexylglycerin

glycerin

helianthus annuus (sunflower) seed oil

isostearyl isostearate

PEG-40 hydrogenated castor oil

phenoxyethanol

propylene glycol

sodium hydroxide

water